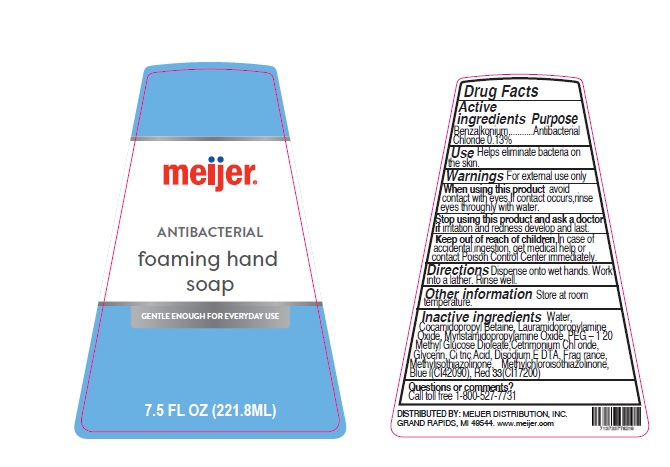 DRUG LABEL: Meijer Antibacterial Foaming Hand Wash
NDC: 79481-1020 | Form: SOAP
Manufacturer: Meijer, Inc.
Category: otc | Type: HUMAN OTC DRUG LABEL
Date: 20250331

ACTIVE INGREDIENTS: BENZALKONIUM CHLORIDE 0.13 mg/100 mL
INACTIVE INGREDIENTS: LAURAMIDOPROPYLAMINE OXIDE; MYRISTAMIDOPROPYLAMINE OXIDE; WATER; POLYETHYLENE GLYCOL 6000; METHYL GLUCOSE DIOLEATE; CETRIMONIUM CHLORIDE; CITRIC ACID MONOHYDRATE; EDETATE DISODIUM; METHYLISOTHIAZOLINONE; GLYCERIN; D&C RED NO. 33; METHYLCHLOROISOTHIAZOLINONE; FD&C BLUE NO. 1; COCAMIDOPROPYL BETAINE

Meijer Antibacterial Foaming Hand Wash

Active Ingredient

Benzalkonium Chloride 0.13%

Purpose

Antibacterial

Use

Helps eliminate bacteria on the skin

Warnings

For external use only

When using this product

avoid contact with eyes. If contact occurs, rinse thoroughly with water.

Stop using this product and ask a doctor if

irritation and redness develop and last

Keep out of reach of children

In case of accidental ingestion get medical help or contact Poison Control Center immediately

Directions

Dispense onto wet hands. Work into a lather. Rinse well.

Other Information

Store at room temperature

Inactive ingredients

Water, Cocamidopropyl Betaine, Lauramidopropylamine Oxide, Myristamidopropylamine Oxide, PEG - 120, Methyl Glucose Dioleate,Cetrimonium Chloride, Glycerin, Citric Acid, Disodium EDTA, Frag rance, Methylisothiazolinone, Methylchloroisothiazolinone, Blue i(CI42090), Red 33(CI17200)

Questions or Comments?

Call toll free 1-800-527-7731

DISTRIBUTED BY

MEIJER DISTRIBUTION, INC. GRAND RAPIDS, MI 49544. www.meijer.com

Principal Display Panel

NDC Code: 79481-1020-8

meijer

ANTIBACTERIAL Foaming Hand Soap

GENTLE ENOUGH FOR EVERYDAY USE

7.5 FL OZ. (221.8ML)